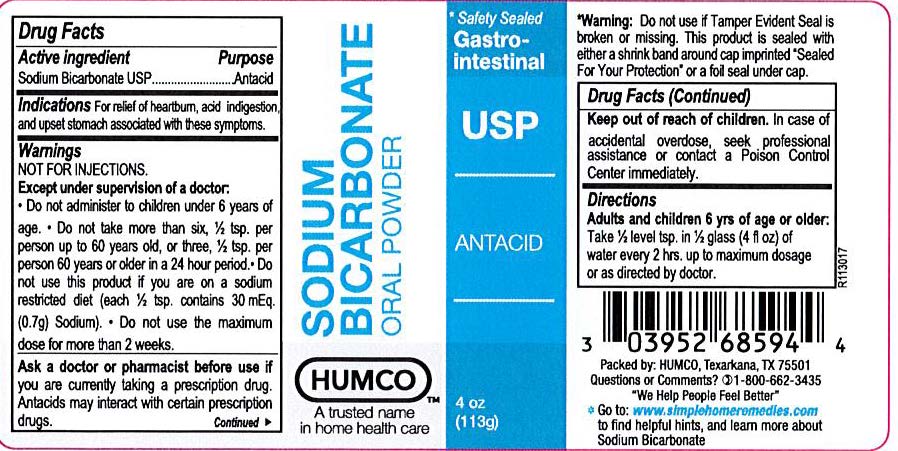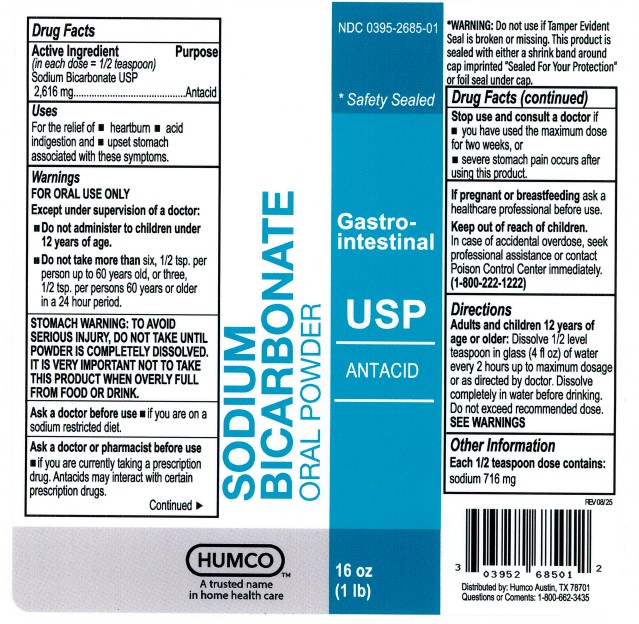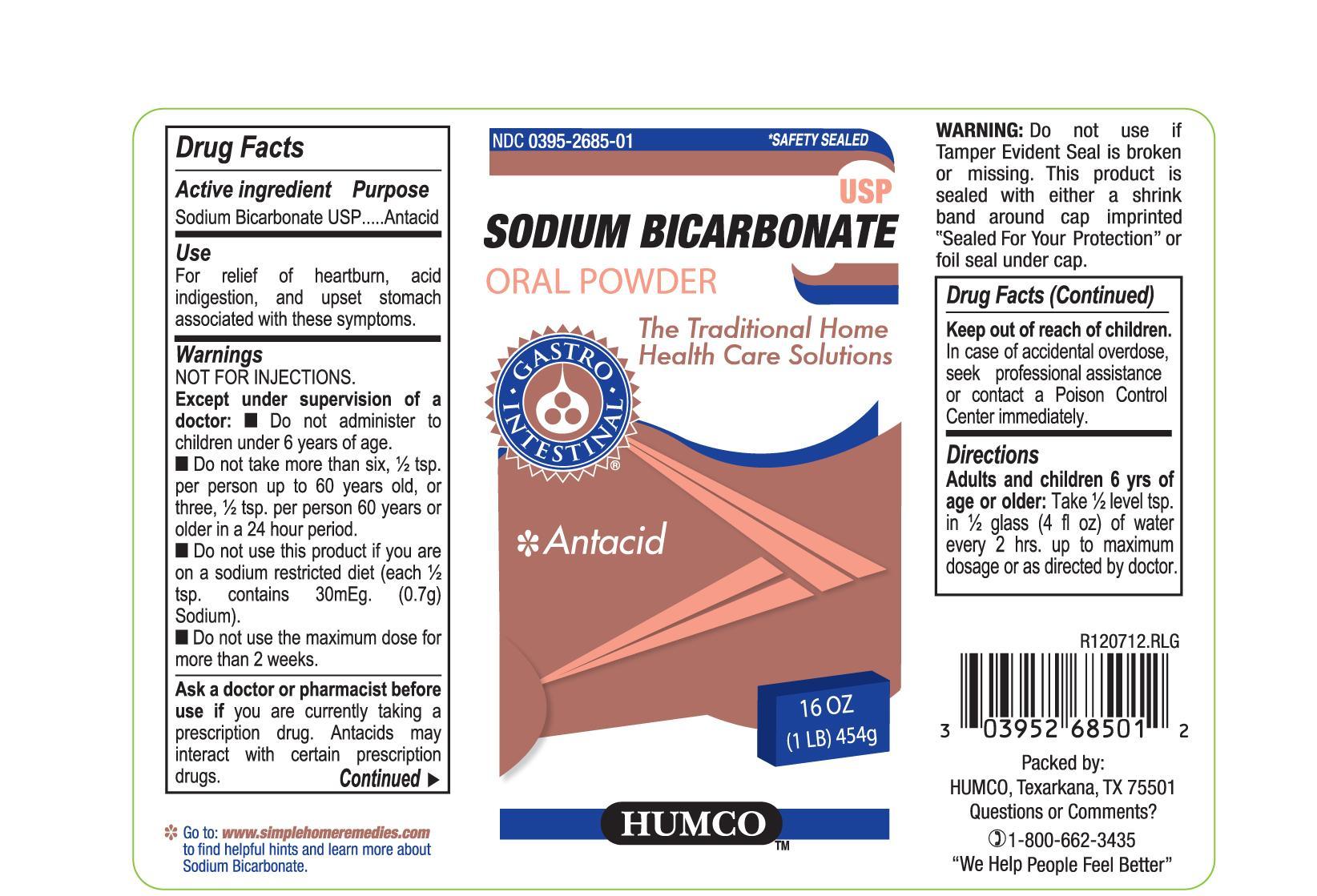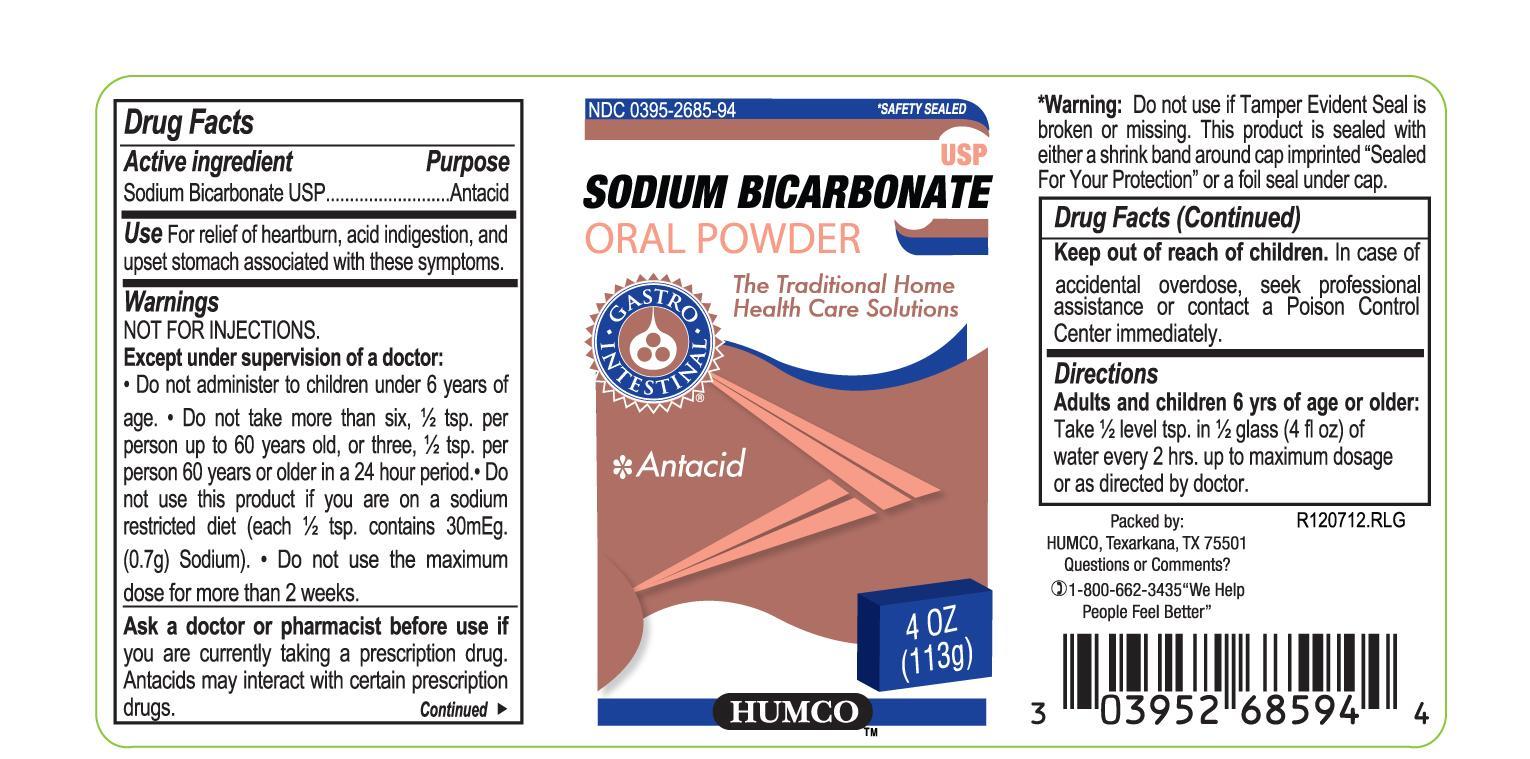 DRUG LABEL: Humco Sodium Bicarbonate
NDC: 0395-2685 | Form: POWDER
Manufacturer: Humco Holding Group, Inc.
Category: otc | Type: HUMAN OTC DRUG LABEL
Date: 20251211

ACTIVE INGREDIENTS: SODIUM BICARBONATE 1000 mg/1 g
INACTIVE INGREDIENTS: WATER

Humco Sodium Bicarbonate, USP

Drug Facts

Active Ingredient

Soduim Bicarbonate, USP

Purpose

Antacid

Use

For relief of heartburn, acid indigestion, and upset stomach associated with these symptoms.

Warnings

FOR ORAL USE ONLY

Except under supervision of a doctor:

Do not administer to children under 12 years of age.

Do not take more than six, 1/2 tsp. per person up to 60 years old, or three 1/2 tsp. per person 60 years or older in a 24 hour period.

STOMACH WARNING: TO AVOID SERIOUS INJURY, DO NOT TAKE UNTIL POWDER IS COMPLETELY DISSOLVED. IT IS VERY IMPORTANT NOT TO TAKE THIS PRODUCT WHEN OVERLY FULL FROM FOOD OR DRINK.

RECENT MAJOR CHANGES

FOR ORAL USE ONLY

Except under supervision of a doctor:

Do not administer to children under 12 years of age.

Do not take more than six, 1/2 tsp. per person up to 60 years old, or three 1/2 tsp. per person 60 years or older in a 24 hour period.

STOMACH WARNING: TO AVOID SERIOUS INJURY, DO NOT TAKE UNTIL POWDER IS COMPLETELY DISSOLVED. IT IS VERY IMPORTANT NOT TO TAKE THIS PRODUCT WHEN OVERLY FULL FROM FOOD OR DRINK.

Ask a doctor or pharmacist before use if you are currently taking a prescription drug. Antacids may interact with certain prescription drugs.

Ask a doctor before use if you are on a sodium restricted diet.

Stop use and consult a doctor if you have used the maximum dose for two weeks, or severe stomach pain occurs after using this product.

Keep out of reach of children.

In case of accidental overdose, seek professional assistance or contact a Poison Control Center immediately.

Directions

Adult and children 12 yrs of age and older:

Dissolve 1/2 level teaspoon in glass (4 fl oz) of water every 2 hours up to maximum dosafe or as directed by doctor. Dissolve completely in water before drinking. Do not exceed recommended dose. SEE WARNINGS.

Inactive ingredients

none

Packae Principal Display Pannel

Label 4 oz

Principal Display Pannel

Label 16 oz